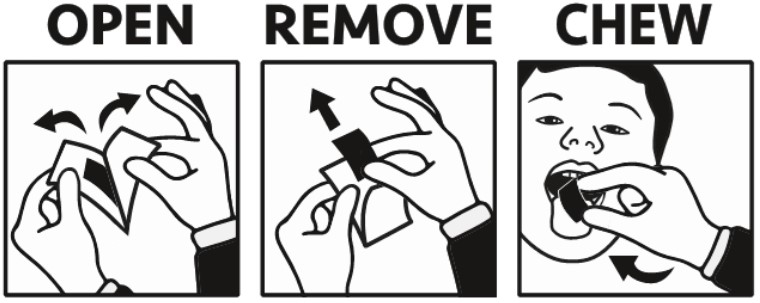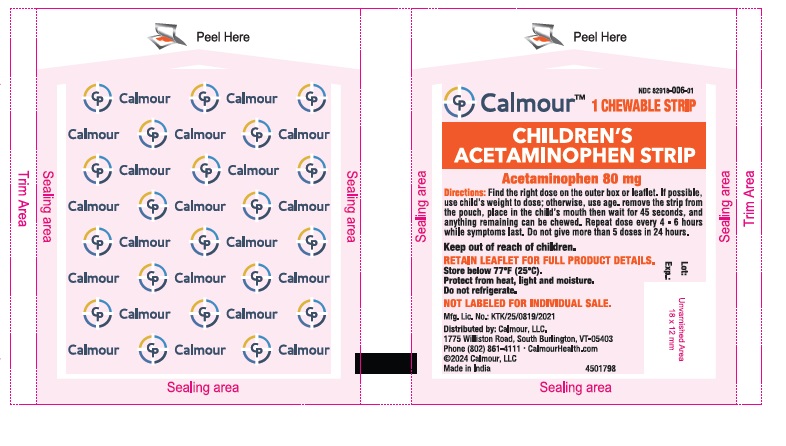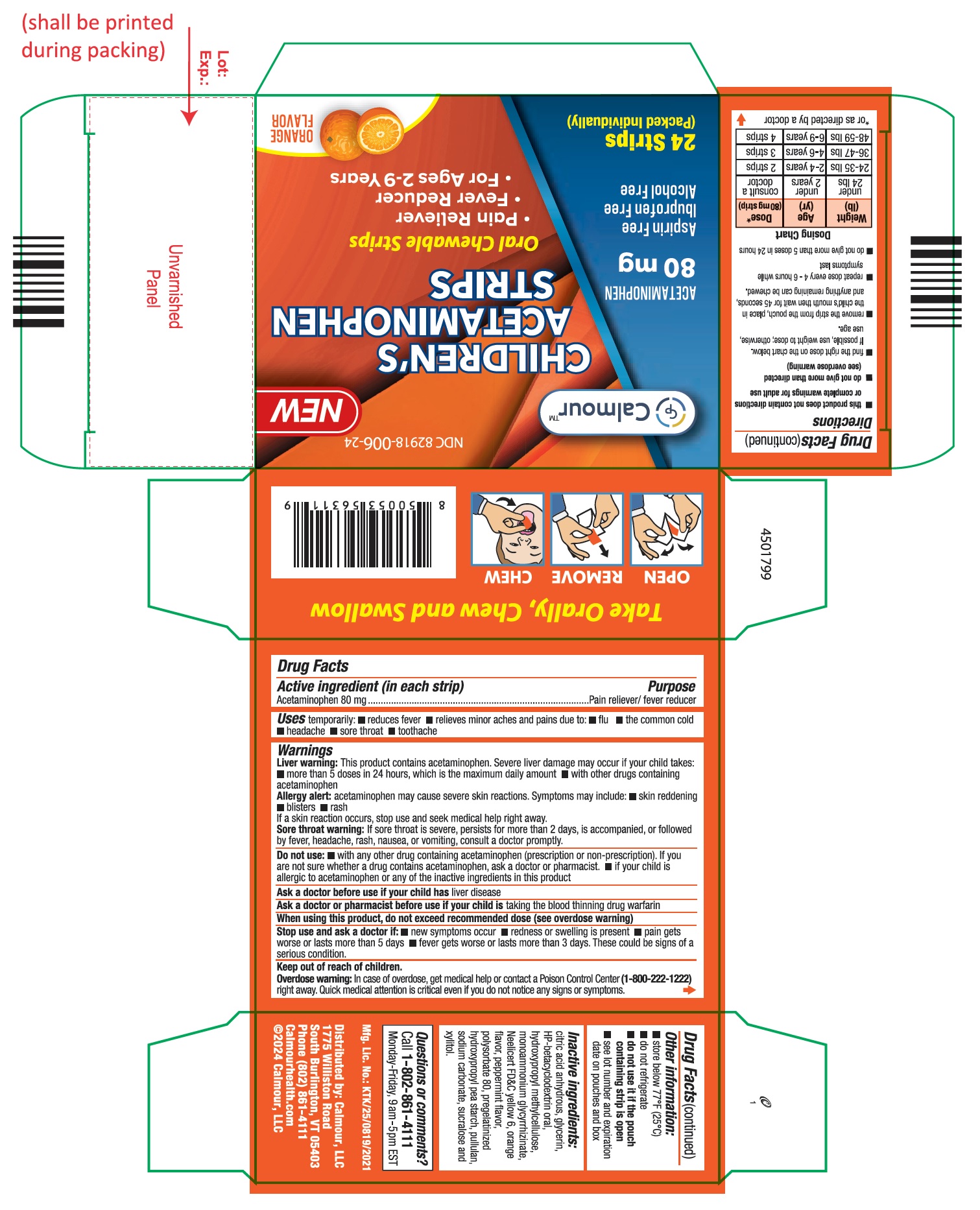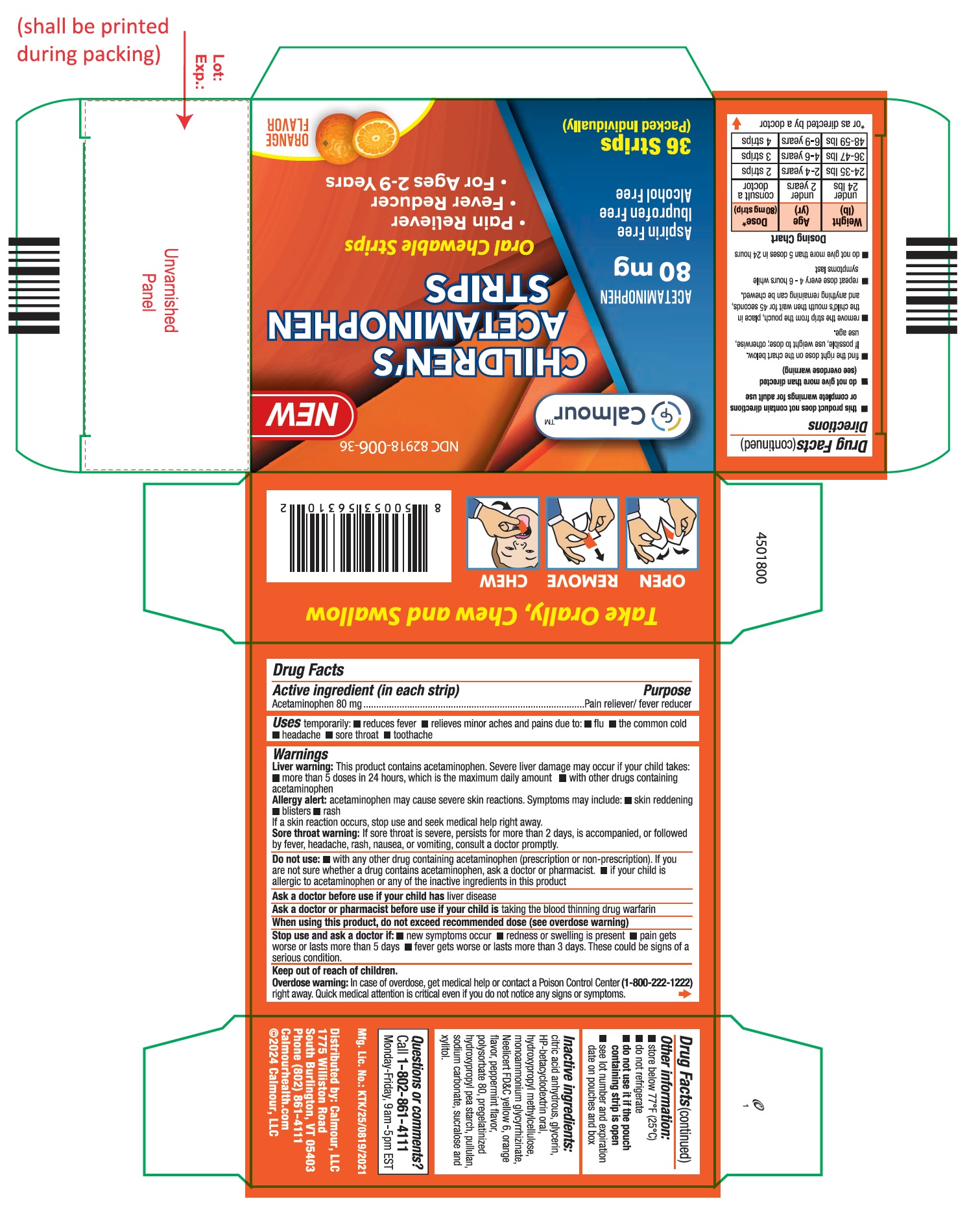 DRUG LABEL: Calmour Childrens Acetaminophen Strips
NDC: 82918-006 | Form: STRIP
Manufacturer: Calmour
Category: otc | Type: HUMAN OTC DRUG LABEL
Date: 20250222

ACTIVE INGREDIENTS: ACETAMINOPHEN 80 mg/1 1
INACTIVE INGREDIENTS: ANHYDROUS CITRIC ACID; GLYCERIN; HYDROXYPROPYL BETADEX; HYPROMELLOSE, UNSPECIFIED; FD&C YELLOW NO. 6; ORANGE; PEPPERMINT; POLYSORBATE 80; PULLULAN; SODIUM CARBONATE; SUCRALOSE; XYLITOL; AMMONIUM GLYCYRRHIZATE; HYDROXYPROPYL CORN STARCH (5% SUBSTITUTION BY WEIGHT)

Active ingredient (in each strip)

Acetaminophen 80 mg

Purpose

Pain reliever/fever reducer

Uses

Temporarily: ■ reduces fever ■ relieves minor aches and pains due to: ■ flu ■ the common cold ■ headache ■ sore throat ■ toothache

Warnings

Liver warning: This product contains acetaminophen. Severe liver damage may occur if your child takes:

- more than 5 doses in 24 hours, which is the maximum daily amount
- with other drugs containing acetaminophen

Allergy alert: acetaminophen may cause severe skin reactions. Symptoms may include:

- skin reddening
- blisters
- rash

If a skin reaction occurs, stop use and seek medical help right away.

Sore throat warning: If sore throat is severe, persists for more than 2 days, is accompanied, or followed by fever, headache, rash, nausea, or vomiting, consult a doctor promptly.

Do not use:

- with any other drug containing acetaminophen (prescription or non-prescription). If you are not sure whether a drug contains acetaminophen, ask a doctor or pharmacist.
- if your child is allergic to acetaminophen or any of the inactive ingredients in this product.

Ask a doctor before use if your child has liver disease.

Ask a doctor or pharmacist before use if your child is taking the blood thinning drug warfarin.

When using this product, do not exceed recommended dose (see overdose warning).

Stop use and ask a doctor if:

- new symptoms occur
- redness or swelling is present
- pain gets worse or lasts more than 5 days
- fever gets worse or lasts more than 3 days

These could be signs of a serious condition.

Keep out of reach of children.

Overdose warning: In case of overdose, get medical help or contact a Poison Control Center (1-800-222-1222) right away. Quick medical attention is critical even if you do not notice any signs or symptoms.

Directions

- this product does not contain directions or complete warnings for adult use
- do not give more than directed (see overdose warning)
- find the right dose on the chart below. If possible, use weight to dose; otherwise, use age.
- remove the strip from the pouch, place in the child's mouth then wait for 45 seconds, and anything remaining can be chewed.
- repeat dose every 4-6 hours while symptoms last
- do not give more than 5 doses in 24 hours

Dosing Chart
Age in Years | Wt in lbs | Number of strips given every 4-6 hours of acetaminophen 80 mg*
under 2 years | < 24 lbs | consult a doctor
2 to under 4 years | 24-35 lbs | 2 strips of 80 mg
4 to under 6 years | 36-47 lbs | 3 strips of 80 mg
6 to under 9 years | 48-59 lbs | 4 strips of 80 mg
Wt: weight; lb: pound; mg: milligram
* or as directed by a doctor

Other information

- store below 77°F (25°C)
- do not refrigerate
- do not use it if the pouch containing strip is open
- see lot number and expiration date on pouch containing strip and box

Inactive ingredients

citric acid anhydrous, glycerin, HP-betacyclodextrin oral, hydroxypropyl methylcellulose, monoammonium glycyrrhizinate, Neelicert FD&C yellow 6, orange flavor, peppermint flavor, polysorbate 80, pregelatinized hydroxypropyl pea starch, pullulan, sodium carbonate, sucralose and xylitol.

Questions or comments?

Call 1-802-861-4111

Monday-Friday, 9 am-5 pm EST

Distributed by:

CALMOUR, LLC

1775 Williston Road

South Burlington, VT 05403

Phone (802) 861-4111

Calmourhealth.com

©2024 Calmour, LLC

PACKAGE LABEL.PRINCIPAL DISPLAY PANEL

Pouch Label

NDC 82918-006-01

CHILDREN'S ACETAMINOPHEN STRIP

CALMOUR

Acetaminophen 80 mg

1 Chewable Strip

POUCH LABEL

CARTON LABEL

NDC 82918-006-24

CHILDREN'S ACETAMINOPHEN STRIPS

Oral Chewable Strip

● Pain Reliever

● Fever Reducer

● For Ages 2-9 Years

ACETAMINOPHEN 80 mg

Aspirin Free

Ibuprofen Free

Alcohol Free

24 Strips

(packed individually)

CARTON LABEL

CARTON LABEL

NDC 82918-006-36

CHILDREN'S ACETAMINOPHEN STRIPS

Oral Chewable Strip

● Pain Reliever

● Fever Reducer

● For Ages 2-9 Years

ACETAMINOPHEN 80 mg

Aspirin Free

Ibuprofen Free

Alcohol Free

36 Strips

(packed individually)

CARTON LABEL